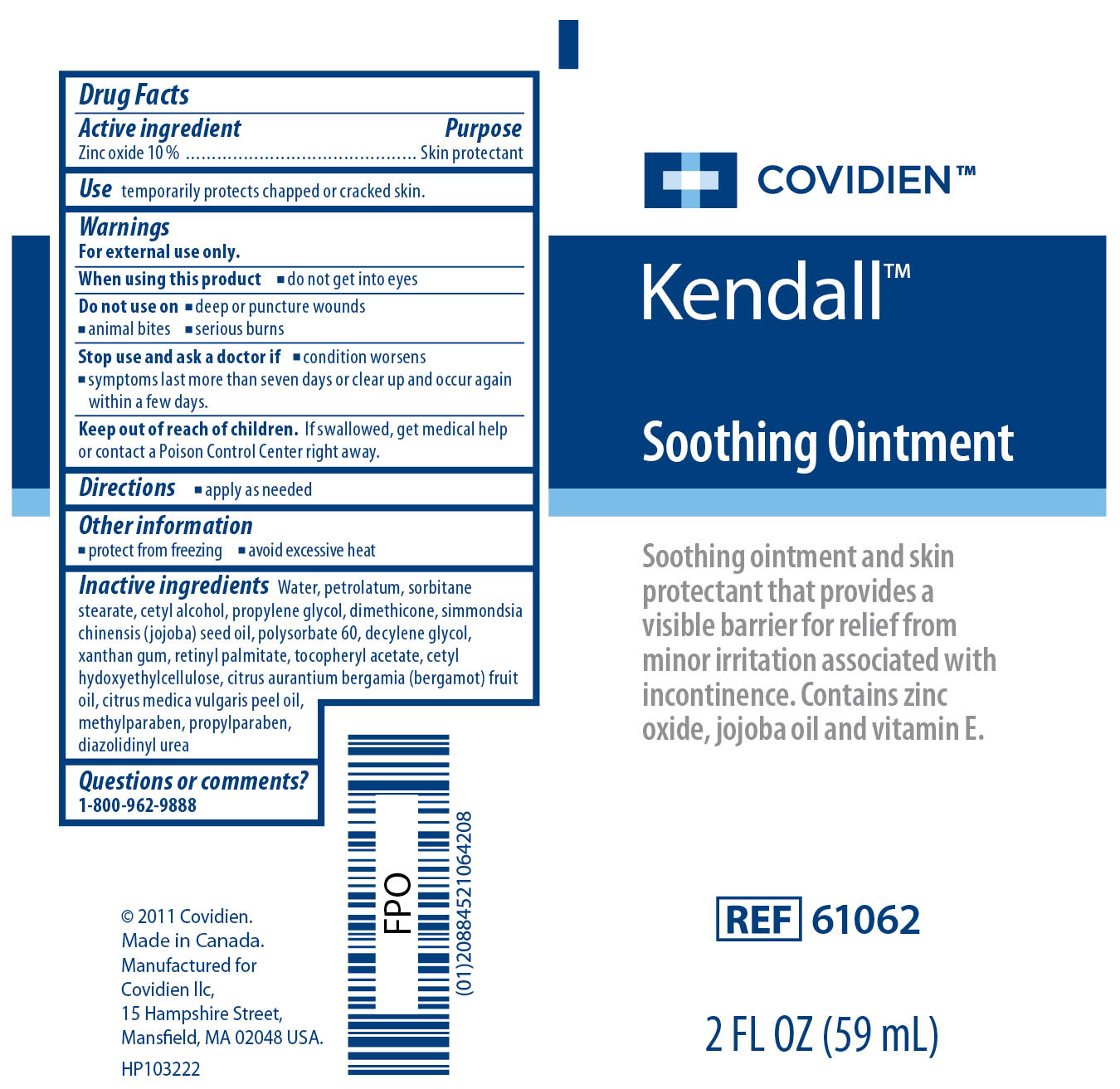 DRUG LABEL: Kendall Soothing
NDC: 28851-695 | Form: OINTMENT
Manufacturer: Covidien Inc.
Category: otc | Type: HUMAN OTC DRUG LABEL
Date: 20110427

ACTIVE INGREDIENTS: Zinc Oxide 10 mL/100 mL
INACTIVE INGREDIENTS: Water; PETROLATUM; SORBITAN MONOSTEARATE; PROPYLENE GLYCOL ; BERGAMOT OIL ; VITAMIN A PALMITATE; ACETATE ION; METHYLPARABEN; PROPYLPARABEN ; DIAZOLIDINYL UREA; CETYL ALCOHOL; DIMETHICONE; JOJOBA OIL; POLYSORBATE 60; 1-DECENE; XANTHAN GUM; CETYL HYDROXYETHYLCELLULOSE (350000 MW)

Kendall Soothing Ointment

Active Ingredient

Zinc oxide 10%

Purpose

Skin protectant

Use

temporarily protects chapped or cracked skin.

Warnings

For external use only.
When using this product

- do not get into eyes

Do not use on

- deep or puncture wounds
- animal bites
- serious burns

Stop use and ask a doctor if

- condition worsens
- symptoms last more than seven days or clear up and occur again within a few days.

Keep out of the reach of children. If swallowed, get medical help or contact a Poison Control Center right away.

Directions

- apply as needed

Other Information

- protect from freezing
- avoid excessive heat

Inactive ingredients

Water, Polysorbate 60, petrolatum, sorbitan stearate, cetyl alcohol, propylene glycol, dimethicone, simmondsia chinensis (jojoba) seed oil, decylene glycol, xanthan gum, cetyl hydroxyethylcellulose, citrus aurantium bergamia (bergamot) fruit oil, citrus medica vulgaris peel oil, retinyl palmitate, tocopheryl acetate, methylparaben, propylparaben, diazolidinyl urea

Questions or comments? 1-800-962-9888

PACKAGE LABEL

Image of Kendall Soothing Ointment 2 Fl oz Label